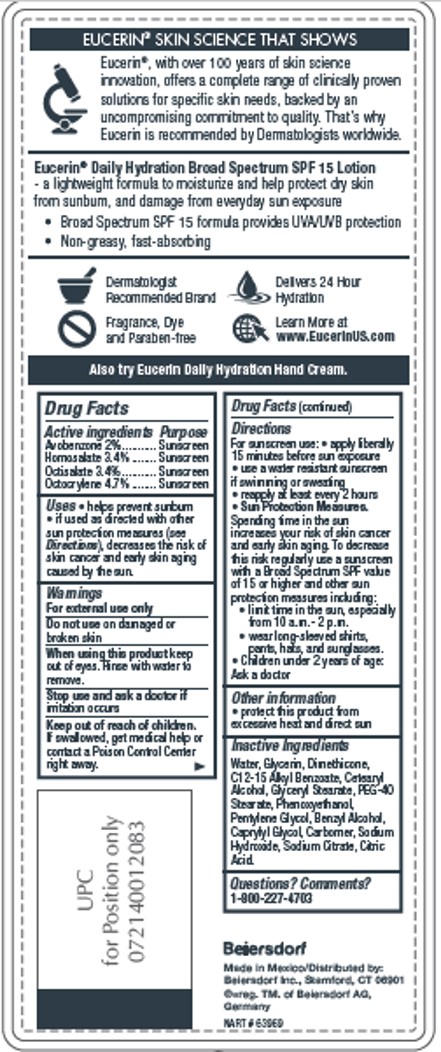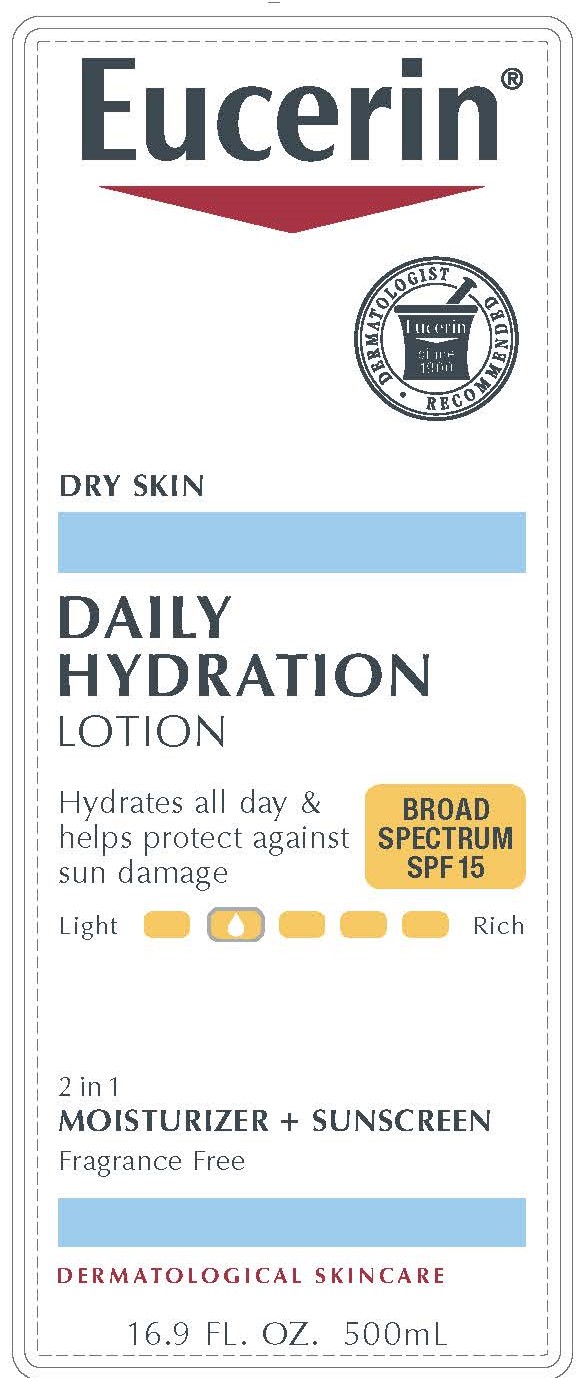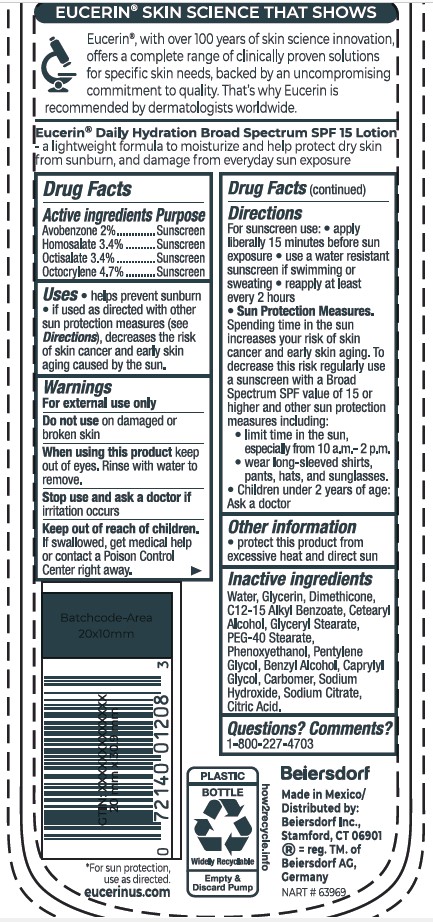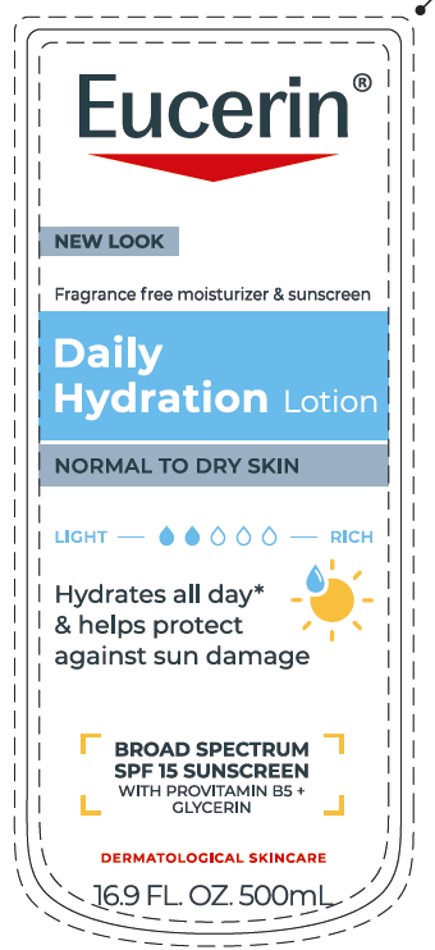 DRUG LABEL: Eucerin Daily Hydration
NDC: 10356-328 | Form: LOTION
Manufacturer: Beiersdorf Inc
Category: otc | Type: HUMAN OTC DRUG LABEL
Date: 20251231

ACTIVE INGREDIENTS: AVOBENZONE 2 g/100 mL; HOMOSALATE 3.4 g/100 mL; OCTISALATE 3.4 g/100 mL; OCTOCRYLENE 4.7 g/100 mL
INACTIVE INGREDIENTS: WATER; GLYCERIN; ALKYL (C12-15) BENZOATE; DIMETHICONE; CETOSTEARYL ALCOHOL; GLYCERYL MONOSTEARATE; PHENOXYETHANOL; PEG-40 STEARATE; PENTYLENE GLYCOL; BENZYL ALCOHOL; CAPRYLYL GLYCOL; SODIUM CITRATE; CITRIC ACID MONOHYDRATE; CARBOMER HOMOPOLYMER TYPE A (ALLYL PENTAERYTHRITOL CROSSLINKED)

Eucerin Daily Hydration Lotion

Active ingredients
Avobenzone 2%

Homosalate 3.4%

Octisalate 3.4%

Octocrylene 4.7%

Purpose
Sunscreens

Uses
• helps prevent sunburn • if used as directed with other sun protection
measures (see Directions), decreases the risk of skin cancer and early skin aging
caused by the sun.

Warnings
For external use only

Do not use on damaged or broken skin

When using this product keep out of eyes.
Rinse with water to remove

Stop use and ask a doctor if irritation occurs

Keep out of reach of children. If swallowed,
get medical help or contact a Poison Control
Center right away.

Directions
For sunscreen use: • apply liberally 15
minutes before sun exposure • use a water
resistant sunscreen if swimming or sweating
• reapply at least every 2 hours
• Sun Protection Measures. Spending time in
the sun increases your risk of skin cancer and
early skin aging. To decrease this risk regularly
use a sunscreen with a Broad Spectrum SPF
value of 15 or higher and other sun protection
measures including:
• limit time in the sun, especially from
10 a.m.-2 p.m.• wear long-sleeved shirts,
pants, hats, and sunglasses.
• Children under 6 months of age: Ask a doctor

Inactive Ingredients

Water, Glycerin, Dimethicone, C12-15 Alkyl Benzoate, Cetearyl Alcohol, Glyceryl Stearate, PEG-40 Stearate, Phenoxyethanol, Pentylene Glycol, Benzyl Alcohol, Caprylyl Glycol, Carbomer, Sodium Hydroxide, Sodium Citrate, Citric Acid.

Questions or comments

1-800-227-4703

PACKAGE LABEL

Eucerin

Daily Hydration
Lotion

Dry Skin

Broad Spectrum SPF 15

Hydrates all day and helps protect against sun damage

2 in 1

Moisturizer and Sunscreen

Fragrance free

Dermatological Skincare

Eucerin

Fragrance free moisturizer and sunscreen

Daily Hydration Lotion

Normal to Dry Skin

Hydrates all day and helps protect against sun damage

Broad spectrum SPF 15 Sunscreen

with Provitamin B5 and Glycerin

Dermatological skincare